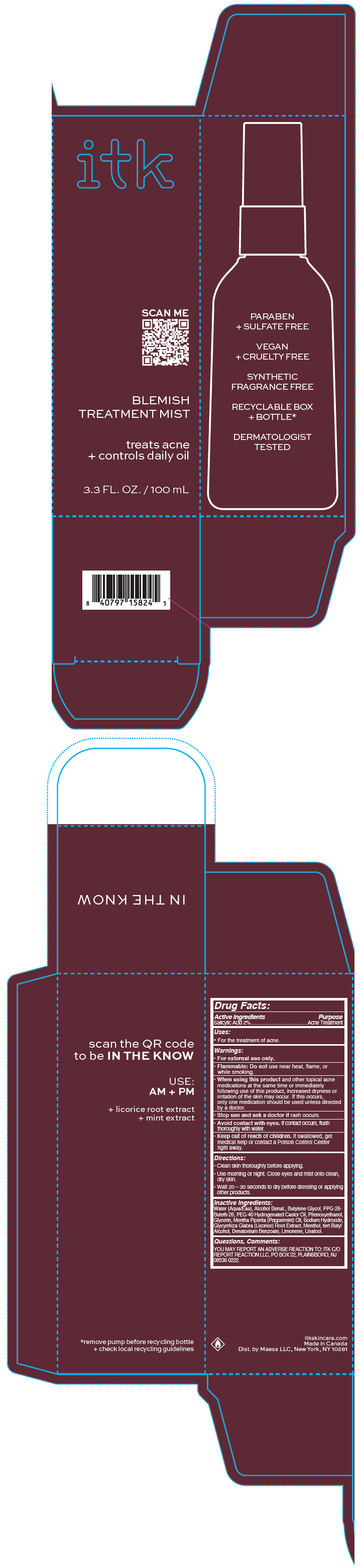 DRUG LABEL: ITK Body Blemish Treatment Mist
NDC: 71899-070 | Form: SPRAY
Manufacturer: MAESA, LLC.
Category: otc | Type: HUMAN OTC DRUG LABEL
Date: 20240119

ACTIVE INGREDIENTS: Salicylic Acid 2 mg/100 mL
INACTIVE INGREDIENTS: DENATONIUM BENZOATE; WATER; ALCOHOL; BUTYLENE GLYCOL; PPG-26-BUTETH-26; POLYOXYL 40 HYDROGENATED CASTOR OIL; PHENOXYETHANOL; GLYCERIN; PEPPERMINT OIL; SODIUM HYDROXIDE; GLYCYRRHIZA GLABRA; MENTHOL, UNSPECIFIED FORM; TERT-BUTYL ALCOHOL; LIMONENE, (+)-; LINALOOL, (+/-)-

ITK Body Blemish Treatment Mist

Drug Facts:

Active Ingredients

Salicylic Acid 2%

Purpose

Acne Treatment

Uses

- For the treatment of acne.

Warnings

- For external use only.
- Flammable: Do not use near heat, flame, or while smoking.

- When using this product and other topical acne medications at the same time or immediately following use of this product, increased dryness or irritation of the skin may occur. If this occurs, only one medication should be used unless directed by a doctor.

- Stop use and ask a doctor if rash occurs.
- Avoid contact with eyes. If contact occurs, flush thoroughly with water.

- Keep out of reach of children. If swallowed, get medical help or contact a Poison Control Center right away.

Directions

- Clean skin thoroughly before applying.
- Use morning or night. Close eyes and mist onto clean, dry skin.
- Wait 20 – 30 seconds to dry before dressing or applying other products.

Inactive Ingredients

Water (Aqua/Eau), Alcohol Denat., Butylene Glycol, PPG-26- Buteth-26, PEG-40 Hydrogenated Castor Oil, Phenoxyethanol, Glycerin, Mentha Piperita (Peppermint) Oil, Sodium Hydroxide, Glycyrrhiza Glabra (Licorice) Root Extract, Menthol, tert-Butyl Alcohol, Denatonium Benzoate, Limonene, Linalool.

Questions, Comments

YOU MAY REPORT AN ADVERSE REACTION TO: ITK C/O REPORT REACTION LLC, PO BOX 22, PLAINSBORO, NJ 08536-0222.

Dist. by Maesa LLC, New York, NY 10281

PRINCIPAL DISPLAY PANEL - 100 mL Bottle Carton

itk

SCAN ME

BLEMISH
TREATMENT MIST

treats acne
+ controls daily oil

3.3 FL. OZ. / 100 mL